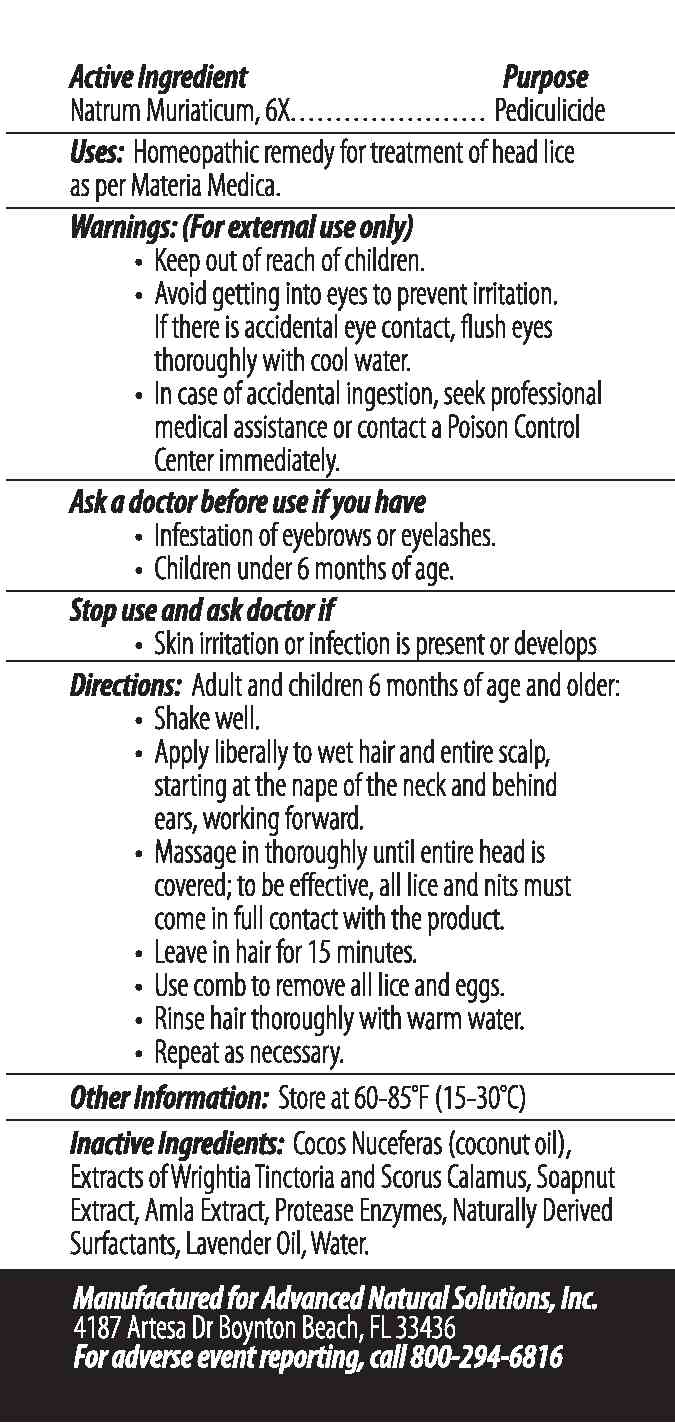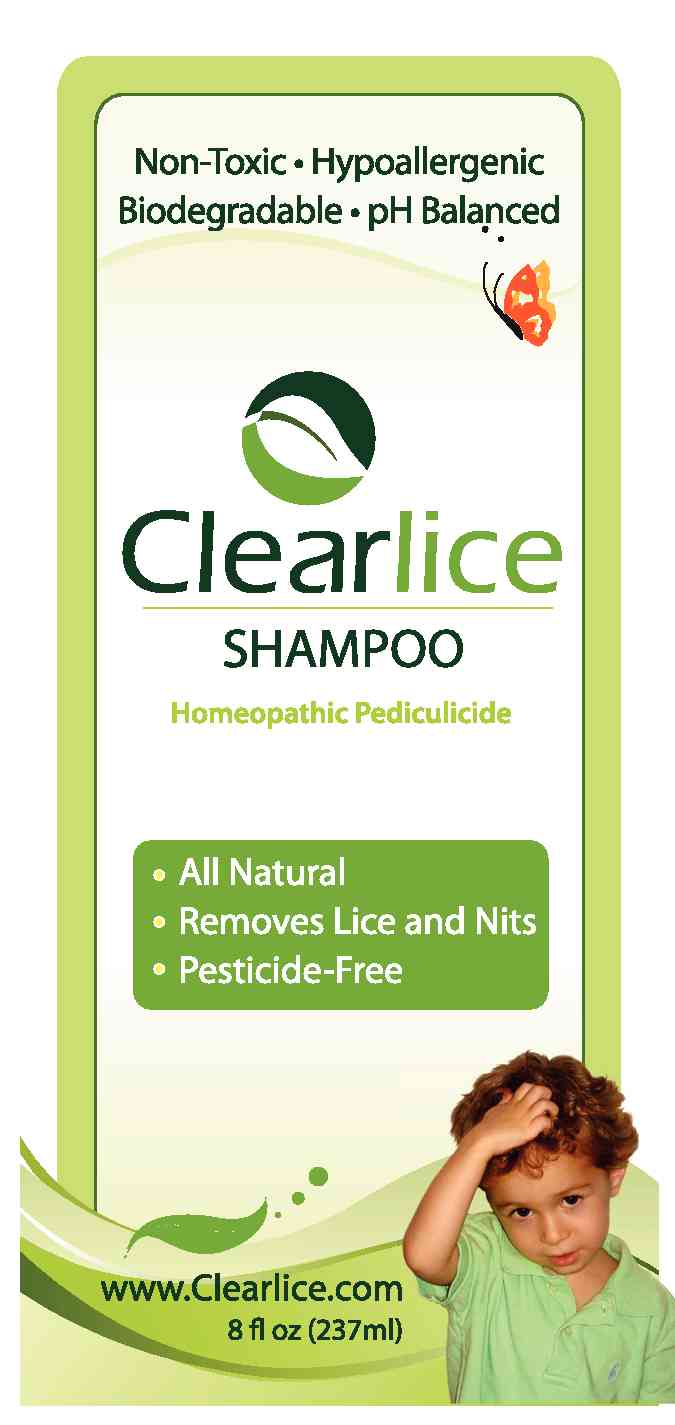 DRUG LABEL: 
                           
NDC: 50126-001 | Form: SHAMPOO
Manufacturer: Advanced Natural Solutions
Category: homeopathic | Type: HUMAN OTC DRUG LABEL
Date: 20091204

ACTIVE INGREDIENTS: SODIUM CHLORIDE 6 [hp_X]/237 mL

Purpose:

Pediculicide

Other Information:

Store at 60-85 Degrees F (15-30 degrees C)

Manufactured for Advanced Natural Solutions, Inc.

4187 Artesa Dr. Boynton Beach FL 33436

For adverse event reporting, call 800-294-6816

Warnings (for external use only):

- Keep out of reach of children
- Avoid getting into eyes to prevent irritation. If there is accidental eye contact, flush eyes thoroughly with cool water.
- In case of accidental ingestion, seek professional medical assistance or contact a Poison Control Center Immediately

Ask a doctor before use if you have:

- Infestation of eyebrows or eyelashes
- Children under 6 months of age

Stop use and ask doctor if:

- Skin irritation or infection is present or develops

INACTIVE INGREDIENT

Cocos Nuceferas (coconut oil), Extracts of Wrightia Tinctoria and Scorus Calamus, Amla Extract, Shikekai Extracts, Protease Enzymes, Lavendar Oil, Water.

INDICATIONS AND USAGE

Directions: Adult and children 6 months of age or older:

- Shake well
- Apply liberally to wet hair and entire scalp, starting at the nape of the neck and behind ears working forward
- Massage in thoroughly until entire head is covered; to be effective, all lice and nits must come in full contact with the product
- Leave in hair for 15 minutes
- Use comb to remove all lice and eggs
- Rinse hair thoroughly with warm water
- Repeat as necessary

Uses: Homeopathic remedy for treatment of head lice as per Materia Medica.

PACKAGE LABEL

Repels Lice and Nits from Coming Back!

Clearlice Conditioner

Homeopathic Pediculicide

Makes hair soft and slick so lice and nits don't stick!

ClearliceFront.jpg

ClearliceBack.jpg